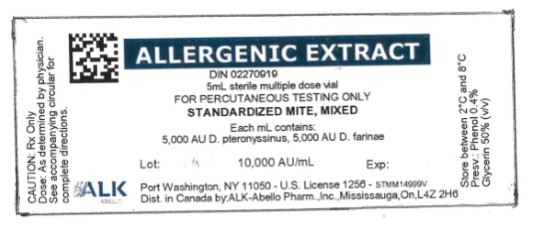 DRUG LABEL: STANDARDIZED MITE, MIXED
NDC: 0268-8116 | Form: INJECTION, SOLUTION
Manufacturer: ALK-Abello, Inc.
Category: other | Type: STANDARDIZED ALLERGENIC
Date: 20251110

ACTIVE INGREDIENTS: DERMATOPHAGOIDES FARINAE 5000 [AU]/1 mL; DERMATOPHAGOIDES PTERONYSSINUS 5000 [AU]/1 mL
INACTIVE INGREDIENTS: SODIUM CHLORIDE 0.005 g/1 mL; SODIUM BICARBONATE 0.00275 g/1 mL; PHENOL 0.004 mL/1 mL; GLYCERIN 0.5 mL/1 mL; HYDROCHLORIC ACID; SODIUM HYDROXIDE

Standardized Mixed Mite 5ml

ALLERGENIC EXTRACT
STANDARDIZED MITE
(Dermatophagoides farinae and Dermatophagoides pteronyssinus)

WARNINGS

Standardized allergenic extract is intended for use by physicians who are experienced in the administration of standardized (AU/mL) allergenic extracts for immunotherapy and the emergency care of anaphylaxis, or for use under the guidance of an allergy specialist. Standardized allergenic extracts are not directly interchangeable with allergenic extracts of the same labeled potency from different manufacturers. The patient must be re-evaluated with the newly selected extract. The initial dose must be based on skin testing as described in the dosage and administration section of this insert. Patients being switched from other types of extracts to standardized allergenic extracts should be started as though they were coming under treatment for the first time. Patients should be instructed to recognize adverse reaction symptoms and cautioned to contact the physician's office if reaction symptoms occur. As with all allergenic extracts, severe systemic reactions may occur. Patients with unstable asthma or steroid dependent asthmatics and patients with underlying cardiovascular disease are at greater risk. In certain individuals, these life-threatening reactions may result in death. Patients should be observed for 20 to 30 minutes following treatment, and emergency measures, as well as personnel trained in their use, should be immediately available in the event of a life-threatening reaction.

This product should not be injected intravenously. Deep subcutaneous routes have proven to be safe. See the warnings, precautions, adverse reactions and over-dosage sections below.

Sensitive patients may experience severe anaphylactic reactions resulting in respiratory obstruction, shock, coma and/or death.

Patients receiving beta-blockers may not be responsive to epinephrine or inhaled bronchodilators. Respiratory obstruction not responding to parenteral or inhaled bronchodilators may require theophylline, oxygen, intubation and the use of life support systems. Parenteral fluid and/or plasma expanders may be utilized for treatment of shock. Adrenocorticosteroids may be administered parenterally or intravenously. Refer to the warnings, precautions and adverse reaction sections below.

Adverse events are to be reported to MedWatch (1-800-FDA-1088), Adverse Event Reporting, Food and Drug Administration, 5600 Fishers Lane, Rockville, MD 20852-9787.

DESCRIPTION

Allergenic Extract Standardized Mite in the accompanying vial is a sterile solution and contains glycerin 50% v/v and phenol 0.4% (preservative). Inert ingredients include sodium chloride for isotonicity and sodium bicarbonates, as a buffer. The mites (D. farinae and/or D. pteronyssinus), used as source material for this extract, were cultured by Biopol Laboratories on a medium consisting of yeast and pork. The whole-body mites were separated from the culture medium and the harvested mites contained less than 1% culture medium material.

Several manufacturers submitted to FDA, intradermal skin test data on Biopol Laboratory’s mite medium extract using patients who were puncture test positive (sum of erythema equal to or greater than 40 mm) to either D. farinae or D. pteronyssinus extracts. By intradermal testing, there was 1 positive (sum of erythema equal to or greater than 20 mm) in 44 individuals at an estimated 1% level of medium contamination of mites, and 4 positives in 40 individuals at an estimated 10% contamination. Two of the individuals who were skin test positive also skin tested by the puncture method with an extract of yeast (Saccharomyces sp) and were positive.

In ten mite sensitive patients, ALK-Abelló, Inc. observed no puncture or intradermal reactions to media from the same source at a carryover concentration equivalent to 1% of the mite extract.

For ease in use, and for lot to lot consistency, potency value is expressed in allergy units per milliliter.

This ELISA standardized mite extract was compared to a mite reference preparation supplied by FDA which was labeled 10,000 AU/mL based on skin testing.^1 The relative potency of this mite extract was determined by ELISA inhibition in comparison to the FDA Mite reference and is labeled in AU's (Allergy Units/mL).^2 Dilutions made from this product can be administered intradermally for testing, or subcutaneously for immunotherapy.

CLINICAL PHARMACOLOGY

Diagnostically (for skin testing) the allergen combines with IgE antibodies fixed to mast cells in the skin.^3 This complexing causes an increase in cellular permeability and degranulation of the mast cells releasing chemical mediators. These mediators (such as histamine) are responsible for a local inflammatory response of wheal and erythema typical of a positive skin test reaction and also, the symptoms commonly associated with allergic disease. The more mediator release, the larger the reaction (wheal and erythema).

Treatment consists of the subcutaneous injection of gradually increasing doses of the allergens to which the patient is allergic. It has been demonstrated that this method of treatment induces an increased tolerance to the allergens responsible for the symptoms on subsequent exposure. Although the exact relationships between allergen, skin sensitizing antibody (IgE) and the blocking antibody (IgG) have not been precisely established, clinically confirmed immunological studies have adduced evidence of the efficacy of hyposensitization therapy.

Numerous controlled studies have demonstrated the clinical efficacy of immunotherapy with cat, dust mites and some pollen extracts.^4 Nevertheless, responses are not uniform but variable, and in a few studies, the majority of the patients reported no appreciable improvement.

INDICATIONS AND USAGE

This product is indicated for the diagnosis and treatment of hypersensitivity in patients with symptoms compatible with dust mite allergy.

Hyposensitization (injection) therapy is a treatment for patients exhibiting allergic reactions to seasonal pollens, dust mites, molds, animal danders, and various other inhalants, in situations where the offending allergen cannot be avoided. Mixtures of standardized mite (D. farinae and D. pteronyssinus) should be considered for treatment of patients who are sensitive to both species.

Prior to the initiation of therapy, clinical sensitivity should be established by careful evaluation of the patient's history confirmed by diagnostic skin testing. Hyposensitization should not be prescribed for sensitivities to allergens which can be easily avoided.

CONTRAINDICATIONS

There are no known absolute contraindications to immunotherapy. However, a patient should not be immunized with preparations of allergens to which the patient has not demonstrated symptoms and positive skin tests. In most cases, immunotherapy is not indicated for those allergens that can be eliminated or minimized by environmental control.

Also, there is some evidence, although inconclusive, that routine immunizations may exacerbate autoimmune diseases.^5,6,7 Hyposensitization should be given cautiously to patients with this predisposition. Patients with severe cardiorespiratory symptoms are at additional risk during a systemic reaction. The physician must weigh the risk to benefit in these cases.

Patients on beta-blockers are not candidates for immunotherapy, as they can be non-responsive to beta-agonists that may be required to reverse a systemic reaction. Also, see BOXED WARNING section.

In the presence of active symptoms such as rhinitis, wheezing, dyspnea, etc., the indications of immunotherapy must be weighed carefully against the risk of temporarily aggravating the symptoms by the injection itself.

WARNINGS

See warnings at the beginning of this package insert. Standardized allergenic extracts are not directly interchangeable with allergenic extracts of the same labeled potency from different manufacturers. The patient must be re-evaluated with the newly selected extract.

A reduction in starting dose is recommended in the following circumstances:

1. Changing to a new lot of extract from the same manufacturer
2. Using product from a different manufacturer
3. Using non-standardized extract or any other change in formula
4. Changing to a product bearing a later expiration date
5. When a prolonged lapse in time has occurred since the last injection

Withhold allergenic extracts temporarily or reduce the dose in patients with any one of the following conditions:

- Severe rhinitis or asthma symptoms;

- Infection or flu accompanied by fever;

- Exposure to excessive amounts of clinically relevant allergen prior to therapy.

Allergenic extracts slowly become less potent with age. During the course of treatment, it may be necessary to continue therapy with a vial of extract bearing a later expiration date. The initial dose of the extract bearing the later expiration date should be lowered to a safe non-reaction-eliciting level. When switching one standardized extract with another, at least 75% reduction in dose is suggested.

Patients should always be observed for at least 20 to 30 minutes after any injection. In the event of a marked systemic reaction such as urticaria, angioedema, wheezing, dyspnea, respiratory obstructions, hypotension and coma, application of a tourniquet above the injection site and administration of 0.2 mL to 1.0 mL (0.01 mg/kg) of Epinephrine Injection (1:1000) is recommended. Maximal recommended dose for children between 2 and 12 years of age is 0.5 mL. The tourniquet should not be left in place without loosening for 90 seconds every 15 minutes. Patients under treatment with beta-blockers may be refractory to the usual dose of epinephrine.

Volume expanders and vasopressor agents may be required to reverse hypotension. Inhalation bronchodilators and parenteral aminophylline may be required to reverse bronchospasm. In cases of respiratory obstruction, oxygen and intubation may be necessary. Life-threatening reactions unresponsive to the above may require cardiopulmonary resuscitation. DO NOT GIVE INTRAVENOUSLY.

Mite Extracts (D. farinae and/or D. pteronyssinus) contain small (<1%) amounts of residual media components (pork and yeast). The physician should proceed with caution when using mite extract in mite sensitive individuals that also demonstrate sensitivity to these media components and only if clearly warranted.

In the presence of active symptoms such as rhinitis, wheezing, dyspnea, etc., the indications of immunotherapy must be weighed carefully against the risk of temporarily aggravating the symptoms by the injection itself. If the protective action of allergenic extract injections is considered essential for the patient's welfare, appropriate symptomatic therapy with antihistaminic, adrenergic or other drugs might be needed either prior to or in conjunction with allergenic extract injections.

PRECAUTIONS

INFORMATION TO PATIENTS:

Patients should be instructed to describe any active allergic symptoms such as rhinitis, wheezing, dyspnea, etc., prior to injection including any late reactions from previous administration. Patients should remain in doctor's office for 20-30 minutes following injections and be instructed to report any local or systemic symptoms before leaving. Also, see ADVERSE REACTIONS and WARNINGS Sections.

If the protective action of allergenic extract injections is considered essential for the patient's welfare, appropriate symptomatic therapy with antihistaminic, adrenergic or other drugs might be needed either prior to or in conjunction with the allergenic extract injections.

GENERAL

1. Store allergenic extracts between 2o - 8oC at all times, even during use.

2. Use sterile precautions. Using a sterile tuberculin syringe, injections are given subcutaneously. A separate syringe must be used for each patient to prevent transmission of hepatitis and other infectious disease.

3. Care must be taken to avoid injecting into a blood vessel. Pull gently on syringe plunger to determine if a blood vessel has been entered (See Warnings).

4. Extracts in 50% glycerin can cause discomfort at the site of the injection during the injection.

5. Standardized concentrates of allergenic extracts must be diluted prior to initiation of immunotherapy.

6. Dilute allergenic extracts may be more potent when diluted with Albumin saline than those which do not contain stabilizers such as albumin.

PREGNANCY - CATEGORY C:

Animal reproduction studies have not been conducted with allergenic extracts. It is also not known whether allergenic extracts can cause fetal harm when administered to a pregnant woman or can affect reproduction capacity.

Controlled studies of hyposensitization with moderate to high doses of allergenic extracts during conception and all trimesters of pregnancy have failed to demonstrate any risk to the fetus or to the mother. However, on the basis of histamine's known ability to contract the uterine muscle, the release of significant amounts of histamine from allergen exposure of hyposensitization overdose should be avoided on theoretical grounds. Therefore, allergenic extracts should be used cautiously in a pregnant woman, and only if the benefit outweighs the risk.

PEDIATRIC USE:

Children can receive the same dose as adults, however, to minimize the discomfort associated with dose volume it may be advisable to reduce the volume of the dose by half and administer the injection at two different sites.

GERIATRIC USE:

Studies in geriatric patients have not been conducted. Physicians should consider risk to benefit of immunotherapy in this patient population.

NURSING MOTHERS:

It is not known if allergens administered subcutaneously appear in human milk. Because many drugs are excreted in human milk, caution should be exercised when allergenic extracts are administered to a nursing woman.

CARCINOGENESIS, MUTAGENESIS, IMPAIRMENT OF FERTILITY:

Long term studies in animals have not been performed.

DRUG INTERACTIONS:

Drugs can interfere with the performance of skin tests.^8

Antihistamines: Response to mediator (histamine) released by allergens is suppressed by antihistamines. The length of suppression varies and is dependent on individual patient, type of antihistamine and length of time the patient has been on antihistamines. The duration of this suppression may be as little as 24 hours to several days.

Tricyclic Antidepressants: These exert a potent and sustained decrease of skin reactivity to histamine which may last for a few weeks.

Beta2 Agonists: Oral terbutaline and parenteral ephedrine, in general, have been shown to decrease allergen induced wheal.

Dopamine: Intravenous infusion of dopamine may inhibit skin test responses.

Beta Blocking Agents: Propranolol can significantly increase skin test reactivity (See WARNINGS).

Other Drugs: Short acting steroids, inhaled beta2 agonists, theophylline and cromolyn do not seem to affect skin test response.

ADVERSE REACTIONS

Local: Reactions at the site of injection may be immediate or delayed. Immediate wheal and erythema reactions are ordinarily of little consequence, but if very large, may be the first manifestation of systemic reaction. If large local reactions occur, the patient should be observed for systemic symptoms for which treatment is outlined below. However, systemic reactions may occur in the absence of large local reactions.

Delayed reactions start several hours after injection with local edema, erythema, itching or pain. They are usually at their peak at 24 hours and usually require no treatment. Antihistamine drugs may be administered orally.

The next therapeutic dose should be reduced to the dose which did not elicit a reaction, and subsequent doses increased more slowly, i.e., use of intermediate dilutions.

Systemic: Reports from regulatory authorities in Sweden to the FDA, indicated that several deaths have been associated with the use of mite extracts. The FDA was subsequently informed that these deaths may have been related to use by physicians untrained in the administration of potent extracts rather than a product defect. It should be noted that anaphylaxis and deaths following the injection of mite and other extracts have also been reported by The British Committee on Safety in Medicine.^9 Fatalities from immunotherapy in the United States since 1945 have been extensively reviewed by Lockey, R F, et al^10, Reid M J et al.^11 and more recently by Bernstein, D. I. et al^23 . With careful attention to dosage and administration, such reactions occur infrequently, but it must be remembered that allergenic extracts are highly potent to sensitive individuals and OVERDOSE could result in anaphylactic symptoms. Therefore, it is imperative that physicians administering allergenic extracts understand and be prepared for the treatment of severe reactions.

Systemic reactions are characterized by one or more of the following symptoms: Sneezing, mild to severe general urticaria, itching other than at the injection site, extensive or generalized edema, wheezing, asthma, dyspnea, cyanosis, hypotension, syncope and upper airway obstruction. Symptoms may progress to shock and death. Patients should always be observed for 20 to 30 minutes after any injection. Volume expanders and vasopressor agents may be required to reverse hypotension. Inhalational bronchodilators and parenteral aminophylline may be required to reverse bronchospasm. Severe airway obstruction, unresponsive to bronchodilator, may require tracheal intubation and use of oxygen. In the event of a marked systemic reaction, application of a tourniquet above the injection site and the administration 0.2 mL to 1.0 mL of Epinephrine Injection (1:1000) is recommended. Maximal recommended dose for children under 2 years of age is 0.3 mL. Maximal recommended dose for children between 2 and 12 years of age is 0.5 mL. The tourniquet should not be left in place without loosening for 90 seconds every 15 minutes.

The next therapeutic injection of extract should be reduced to the dose which did not elicit a reaction, and subsequent doses increased more slowly, i.e., use of intermediate dilutions.

OVERDOSE

Signs and symptoms of overdose are typically local and systemic reactions. For a description and management of overdose reactions, refer to "Adverse Reactions" section above.

DOSAGE AND ADMINISTRATION

Parenteral drug products should be inspected visually for particulate matter and discoloration prior to administration whenever solution and container permit.

When diluting bulk extracts, use of either Sterile Diluent for Allergenic Extracts or Sterile Diluent for Allergenic Extracts Normal Saline with HSA is recommended. Dilutions should be made with sterile disposable syringes using aseptic technique. Commonly 10 fold dilutions are used to achieve a desired concentration for intradermal testing or initiation and continuation of immunotherapy. For example, transferring 0.5 mL of a 10,000 AU/mL extract into 4.5 mL of diluent will yield 5 mL of extract @ 1,000 AU/mL. Prepare as many additional serial dilutions as necessary to reach the appropriate concentration.

Care should be exercised to avoid cross contamination of allergens if mixing with other allergenic extracts. The use of separate syringes for each allergen and diluent when compounding patient mixes is recommended.

Diagnosis - In diagnosing the sensitive individual, the symptom history must be associated with exposure to the allergen. Skin testing is used in conjunction with a definitive history for diagnosing individual sensitivities.

An excellent method of recording results is to cover the skin reaction with transparent tape, outline the erythema first then the wheal with an indelible pen, then remove the tape and transfer it to the patient's permanent record. For preferred results, it is recommended that the actual measurement of the extent of both responses be recorded. This can be accomplished by measuring the longest erythema diameter, then selecting the mid - point of that line and measuring at a 90° angle to that line to determine the orthogonal diameter. The sum of these two measurements is the sum of erythema (ƩE); the sum of wheal diameters is determined in a similar manner.

Patient's response is graded on the basis of the size of erythema and/or wheal.

Percutaneous (prick/scratch/puncture) test:

Prick, scratch, or puncture skin tests should be performed initially using an extract specially made for this purpose. The usual dose is one drop.

In a skin test study of 10 patients who were determined to be allergic to mite (D. farinae), the mean puncture test (using a bifurcated needle) to a solution containing 10,000 AU/mL had a sum of erythema of 73 mm (range 43 - 138 mm) and a sum of wheal of 17 mm (range 7 - 31 mm).

In another skin test study of 11 patients who were determined to be allergic to mite (D. pteronyssinus), the mean puncture test (using a bifurcated needle) to a solution containing 10,000 AU/mL had a sum of erythema of 84 mm (range 56 - 112 mm) and a sum of wheal of 20 mm (range 7 - 33 mm).

What follows are general guidelines for percutaneous testing. Different devices and/or techniques influence the size of the reaction, therefore it is important to refer to the device manufacturer's or distributor's instructions when grading reactions.

0 No wheal. Erythema absent or very slight (not more than 1 mm in diameter).

+ Wheal absent or very slight erythema present (not more than 3 mm diameter).

++ Wheal not more than 3 mm diameter, or erythema not more than 5 mm diameter.

+++ Wheal between 3 mm and 5 mm in diameter with erythema. Possible pseudopodia and itching.

++++ Any larger reaction with itching and possible pain.

Intradermal test:

On the forearm or upper outer aspect of the arm, using a 26 - 27 gauge, short bevel needle, inject intradermally .05 mL of the intradermal test solution. Skin whealing responses should be observed 10 - 20 minutes after administering the test.

In a skin test study of the 10 mite puncture reactive patients (D. farinae) described above, the mean intradermal dose for ƩE = 50 mm was 0.01 AU/mL (range = <0.0003 to 0.4 AU/mL).

In the skin test study of the 11 mite puncture reactive patients (D. pteronyssinus) described above, the mean intradermal dose for ƩE = 50 mm was 0.006 AU/mL (range = <0.0007 to 0.05 AU/mL).

Intradermal testing should start with a dilute solution, usually in the range of 1 AU or less.

Glycerinated extracts diluted for intradermal testing may be diluted at least 25 fold to less than 2% glycerin (by volume) as glycerin above this level can cause false positive intradermal skin tests.

A negative skin test is one where the sum of erythema was 0 or equal to the sum of the wheal. As a negative control, the diluent should be tested and included in the interpretation of the skin reactions.

0 No increase in size of bleb since injection. No erythema.

+ An increase in size of bleb and a wheal not more than 5 mm diameter with associated erythema.

++ Wheal between 5 mm and 8 mm in diameter with erythema.

+++ Wheal between 8 mm and 12 mm in diameter with erythema and possible pseudopodia, itching or pain.

++++ Any larger reaction with itching and pain and possible diffuse blush of the skin surrounding the reaction area.

Immunotherapy - Starting dose for immunotherapy is related directly to a patient's sensitivity as determined by carefully executed skin testing. Degree of sensitivity can be established by determination of D50 (the intradermal dose, base three, that produces a ƩE = 50 mm).^1

A general rule is to begin at 1/10 of the dose that produces sum of erythema of 50 mm (approximately a 2+ positive skin test reaction). For example, if a patient exhibits a 2+ intradermal reaction to 1 AU/mL, the first dose should be no higher than 0.05 mL of 0.1 AU/mL. Dosage may be increased by 0.05 mL each time until 0.5 mL is reached, at which time the next 10-fold more concentrated dilution can be used, beginning with 0.05 mL, if no untoward reaction is observed. (See beginning of DOSAGE AND ADMINISTRATION section for instructions in preparing dilutions of concentrates.)

If a tolerated dose of allergenic extract has been established, the initial dose from the new extract should be reduced by 75% of the previously well tolerated dose (see also Precautions).

Interval between doses in the early stages of immunotherapy is no more than once to twice a week, and may gradually be increased to once every two weeks. Generally, maintenance injections may be given as infrequently as once every two weeks to once a month. The progress of patients on immunotherapy should be closely monitored. If improvement is realized a usual course of treatment may be from 3 to 5 years. If progress is unsatisfactory for a year or more, discontinuation of immunotherapy should be considered.

Injections are given subcutaneously preferably in the arm. It is advantageous to give injections in alternate arms and routinely in the same area. In some patients, a local tolerance to the allergen may develop thus preventing a possible severe local reaction.

After inserting the needle, but before injecting the dose, pull plunger of the syringe slightly, if blood returns in the syringe, discard the syringe and contents and repeat injection at another site.

Bulk concentrated extracts must be diluted for initial therapy and intradermal skin testing. For recommended diluent, refer to the beginning of the DOSAGE AND ADMINISTRATION section.

Use standard aseptic precautions when making dilutions. The first dose of the new extract should be reduced at least 50% - 75% of the amount of the dosage from the previous extract.

Stability studies for diluted and undiluted forms of this product are not complete. Indications are the undiluted product will retain its potency under recommended storage conditions at least until the expiration date on the vial label is reached. It is recommended that minimal amounts of the concentrate be diluted so that the diluted product is used up within a relatively short period of time, i.e., preferably not more than four weeks.

HOW SUPPLIED

For percutaneous testing, 5 mL vial, 10,000 AU/mL in glycerin 50% (V/V).

For immunotherapy, 10 mL, 30 mL and 50 mL vials of bulk concentrate, 10,000 AU/mL in glycerin 50% (V/V).

STORAGE: To maintain stability of allergenic extracts, proper storage conditions are essential. Bulk concentrates and diluted extracts are to be stored at 2o to 8o C even during use. Bulk or diluted extracts are not to be frozen. Do not use after the expiration date shown on the vial label.

REFERENCES

^1Turkeltaub, P. C. et al. Office of Biologics Research and Review skin test method for evaluation of subject sensitivity to standardized allergenic extracts and for assignment of allergy units to reference preparations using the ID50EAL method. FDA OBRR Methods of the Allergenic Products Branch. 1986.

^2 Anon. ELISA Competition Assay: Quantitative determination of relative potency of Allergenic Extracts. FDA CBER Methods of the Allergenics Products Testing Laboratory. 1993.

^3 Norman, P. S. The clinical significance of IgE. Hosp. Prac. 1975; 10:41-49.

^4 VanMetre, T. E. and Adkinson, N. F. Immunotherapy for aeroallergen disease. In: Middleton et al. Allergy Principles and Practice 3rd Ed. St. Louis: CV Mosby, 1988:1327.

^5 Umetsu, D. T. et al. Serum sickness triggered by anaphylaxis: a complication of immunotherapy. J. Allergy Clin. Immunol. 1985; 76:713.

^6 Phannphak, P. and Kohler, P. F. Onset of polyarteritis nodosa during allergic hyposensitization treatment. Am. J. Med. 1980; 68:479.

^7 Kohler, P. F. Immune complexes and allergic disease. In: Middleton et al. Allergy Principles and Practice 3rd Ed. St. Louis: CV Mosby, 1988:167.

^8 Bousquet, J.: In vivo methods for the study of allergy: skin test, techniques, and interpretation. In: Middleton et al: Allergy Principles and Practice 3rd Ed. St. Louis: CV Mosby, 1988:167.

^9 Committee on the Safety of Medicines. CSM update: desensitizing vaccines. Brit. Med. J. 1986; 293:948.

^10 Lockey, R. F. et al. Fatalities from immunotherapy(IT) and skin testing (ST). J. Allergy Clin. Immunol. 1987; 79:660.

^11 Reid M J et al. Survey of fatalities from skin testing and immunotherapy 1985-1989. J. Allergy Clin. Immunol. 1993; 92:6.

^12Bernstein DI, Wanner M, Borish L, Liss GM: Immunotherapy Committee, American Academy of Allergy, Asthma and Immunology. Twelve-year survey of fatal reactions to allergen injections and skin testing: 1990-2001. J Allergy Clin Immunol. 204 Jun;113(6):1129-36.

Distributed in Canada by:
Alk-Abelló Pharmaceuticals, Inc.
#35-151 Brunel Road
Mississauga, Ontario Canada, L4Z 2H6

Revision: July 2016
©ALK-Abelló, Inc. 188L

PACKAGE LABEL

Allergenic Extract
5mL sterile multiple dose vial
Standardized Mite, Mixed
Each mL contains:
5,000 AU D. pteronyssinus, 5,000 AU D. farinae
10,000 AU/mL